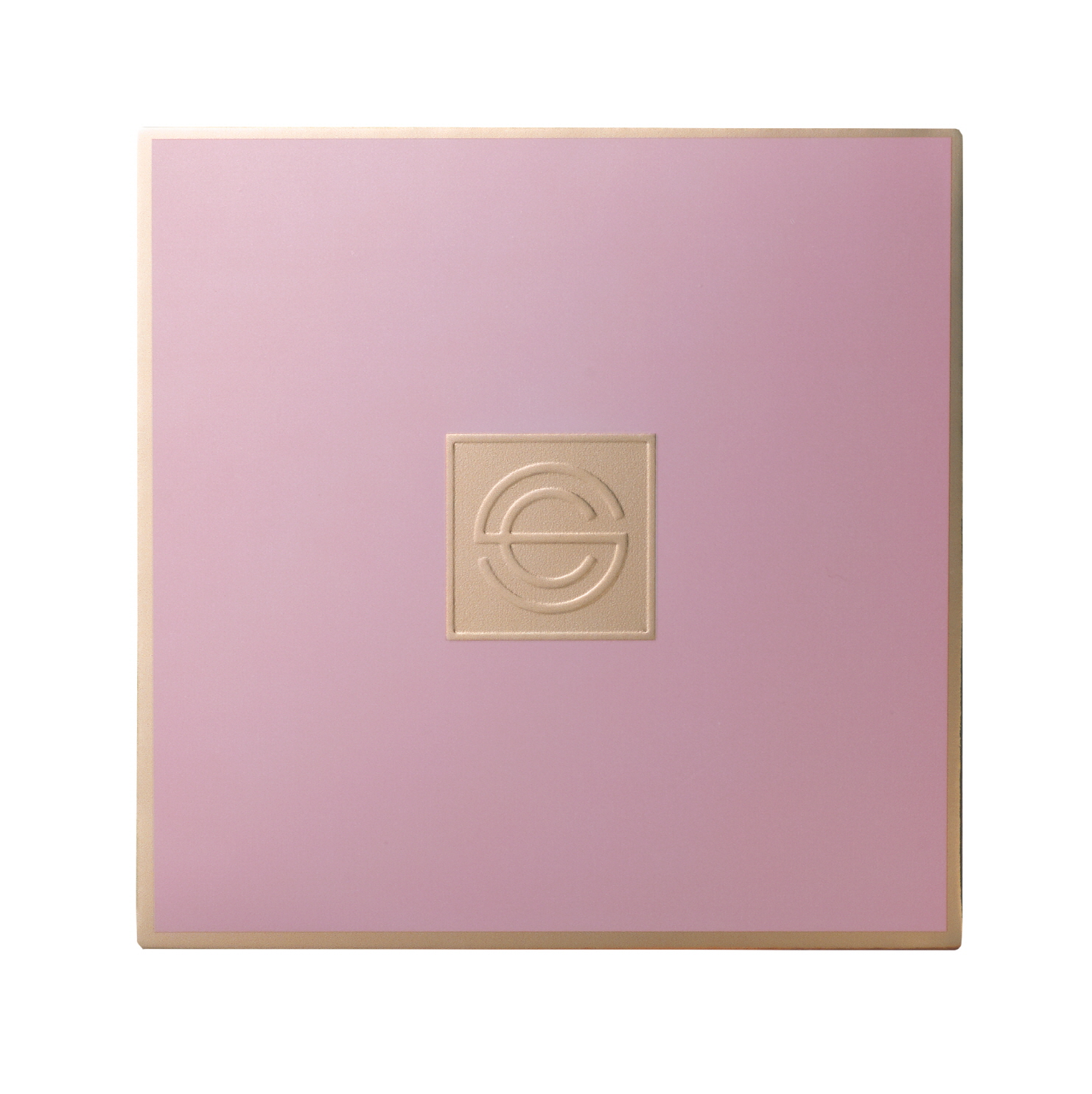 DRUG LABEL: DPC PINK AURA CUSHION NO.21
NDC: 71673-0007 | Form: LIQUID
Manufacturer: MSCO
Category: otc | Type: HUMAN OTC DRUG LABEL
Date: 20170824

ACTIVE INGREDIENTS: OCTINOXATE 7 g/100 g; AMILOXATE 3 g/100 g; OCTISALATE 3 g/100 g; BEMOTRIZINOL 1.5 g/100 g; TITANIUM DIOXIDE 13.3 g/100 g
INACTIVE INGREDIENTS: WATER

ACTIVE INGREDIENT

Titanium Dioxide, Ethylhexyl Methoxycinnamate, Ethylhexyl Salicylate, Isoamyl p-Methoxycinnamate, Bis-Ethylhexyloxyphenol Methoxyphenyl Triazine, Adenosine

INACTIVE INGREDIENT

Water, Butylene Glycol, etc.

PURPOSE

Sun block, Skin whitening, Wrinkle reducer

keep out or reach of the children

INDICATIONS AND USAGE

Take the puff and press it into the cushion, then tap it all round your face to spread it evenly on your face.

Do not use on damaged or broken skin.
When using this product
• Avoid contact with eyes. If contact occurs, rinse eyes thoroughly with water.
Stop use if following symptoms occur. (Continuing in usage may increase symptoms, ask doctor.)
1) If any red spots, swelling, itching, or skin irritation develops.

2) If direct sunlight causes irritation

Keep out of reach of children
• Do not swallow. In case of accidental ingestion, get medical help or contact a Poison Control
Center right away.
Store at room temperature
• Close lid after use – possibility of contamination may exists if displaced contents are replaced back to container.

DOSAGE AND ADMINISTRATION

for external use only